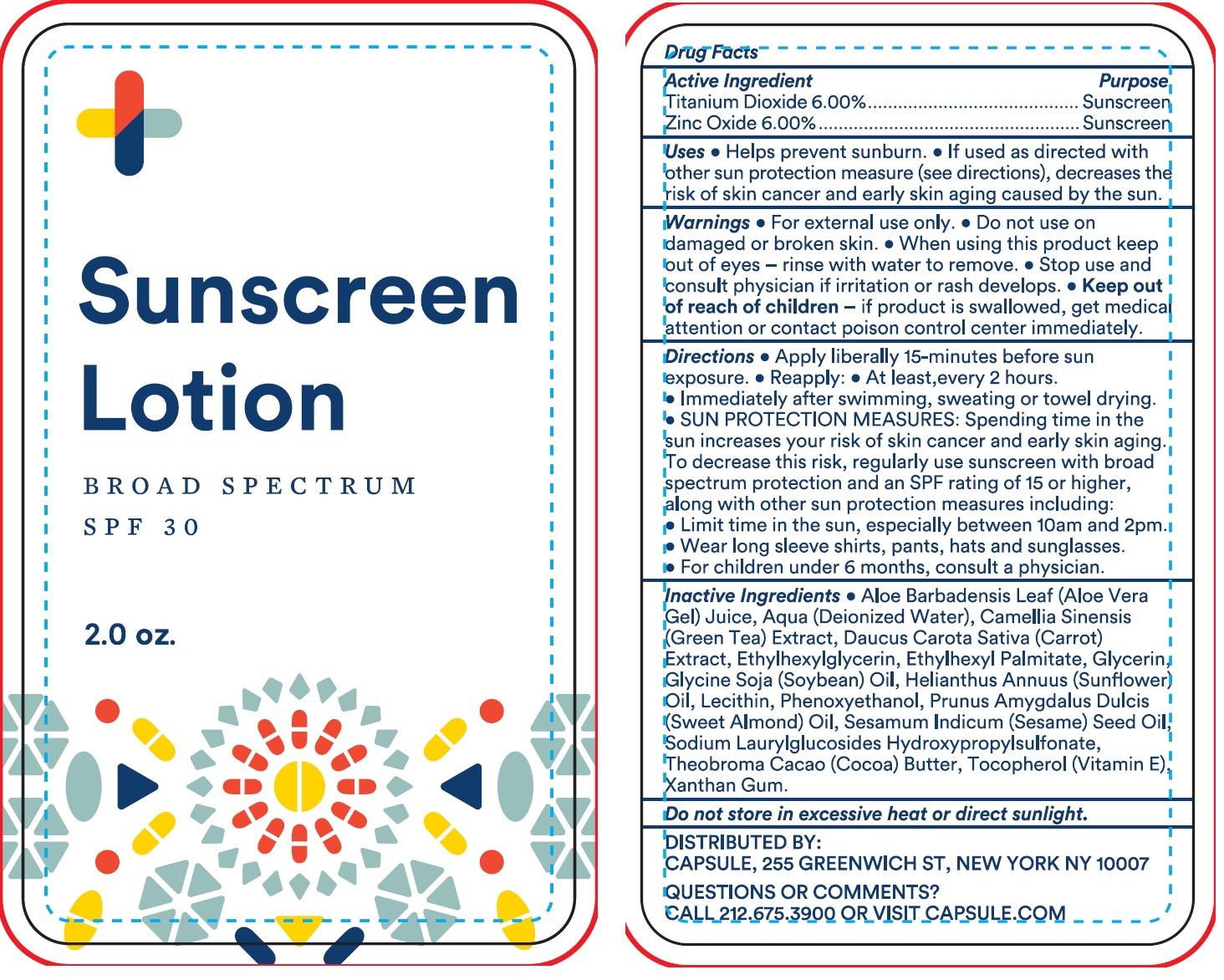 DRUG LABEL: Sunscreen Broad Spectrum SPF 30
NDC: 70469-142 | Form: LOTION
Manufacturer: Capsule Corporation
Category: otc | Type: HUMAN OTC DRUG LABEL
Date: 20200612

ACTIVE INGREDIENTS: TITANIUM DIOXIDE 60 mg/1 mL; ZINC OXIDE 60 mg/1 mL
INACTIVE INGREDIENTS: ALOE VERA LEAF; WATER; GREEN TEA LEAF; CARROT; ETHYLHEXYLGLYCERIN; ETHYLHEXYL PALMITATE; GLYCERIN; SOYBEAN OIL; HELIANTHUS ANNUUS FLOWERING TOP; PHENOXYETHANOL; ALMOND OIL; SESAME OIL; COCOA; TOCOPHEROL; XANTHAN GUM

Sunscreen lotion Broad Spectrum SPF 30

Active Ingredient

Titanium Dioxide 6.00%

Zinc Oxide 6.00%

Purpose

Sunscreen

Uses

- Helps prevent sunburn.
- If used as directed with other sun protection measures (see directions), decreases the risk of skin cancer and early skin aging caused by the sun.

Warnings

- For external use only.

Do not use

- on damaged or broken skin.

When using this product

keep out of eyes

- rinse with water to remove.

Stop use and consult physician

- if irritation or rash develops.

Keep out of reach of children

- if product is swallowed, get medical attention or contact poison control center immediately.

Directions

- Apply liberally 15-minutes before sun exposure.
- Reapply:
- At least,every 2 hours.
- Immediately after swimming, sweating or towel drying.
- SUN PROTECTION MEASURES: Spending time in the sun increases your risk of skin cancer and early skin aging. To decrease this risk, regularly use sunscreen with broad spectrum protection and an SPF rating of 15 or higher, along with other sun protection measures including:
- Limit time in the sun, especially between 10am and 2pm.
- Wear long sleeve shirts, pants, hats and sunglasses.
- For children under 6 months, consult a physician.

Inactive Ingredients

- Aloe Barbadensis Leaf (Aloe Vera Gel) Juice, Aqua (Deionized Water), Camellia Sinensis (Green Tea) Extract, Daucus Carota Sativa (Carrot) Extract, Ethylhexylglycerin, Ethylhexyl Palmitate, Glycerin, Glycine Soja (Soybean) Oil, Helianthus Annuus (Sunflower) Oil, Lecithin, Phenoxyethanol, Prunus Amygdalus Dulcis (Sweet Almond) Oil, Sesamum Indicum (Sesame) Seed Oil, Sodium Laurylglucosides Hydroxypropylsulfonate, Theobroma Cacao (Cocoa) Butter, Tocopherol (Vitamin E) Xanthan Gum.

Do not store in excessive heat or direct sunlight.